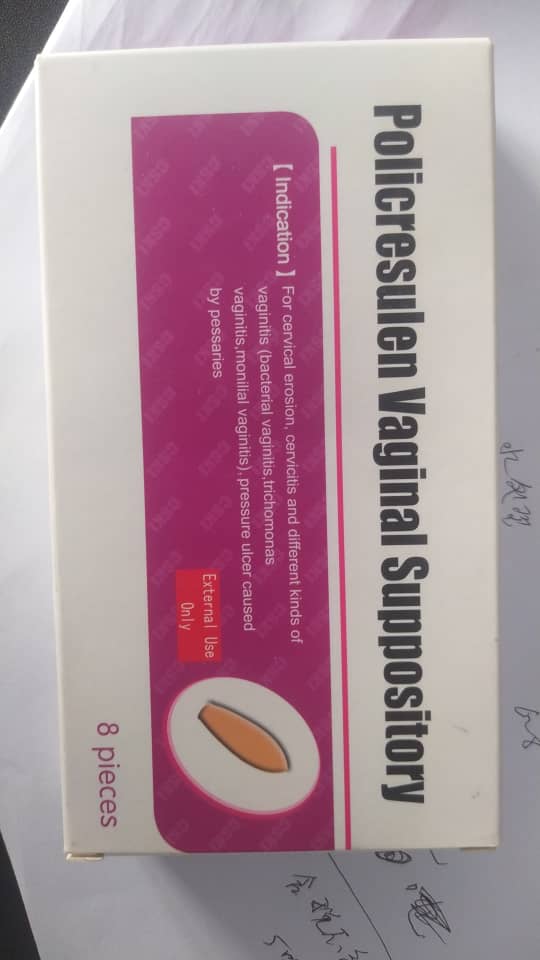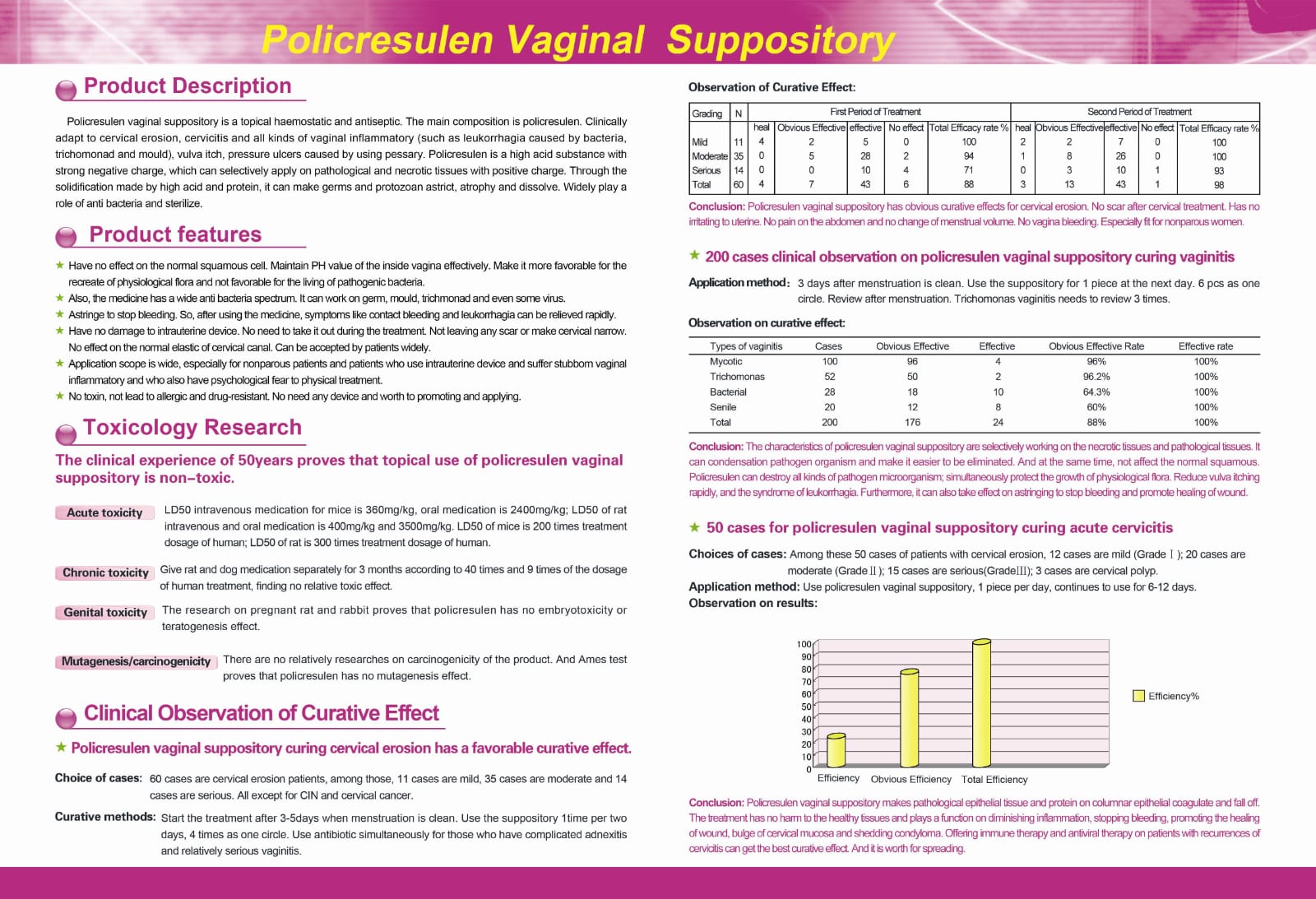 DRUG LABEL: Jujiafenhuangquan Yindaoshuan
NDC: 84149-0042 | Form: SUPPOSITORY
Manufacturer: Heilongjiang Tianlong Pharmaceutical Co Ltd
Category: prescription | Type: HUMAN PRESCRIPTION DRUG LABEL
Date: 20240509

ACTIVE INGREDIENTS: POLICRESULEN 90 mg/1 U
INACTIVE INGREDIENTS: WATER

INSTRUCTIONS FOR USE

78 cases of cervical erosion patients were examined by TCT and HPV, excluded the cervical high intraepithelial lesions and human papillomavirus infection. Then treat with Policresulen Vaginal Suppository. The cervical condition and erosion degree were recorded clearly before treatment. Before sleeping, one suppository was put into the deep vagina, once every other day, two boxes as one course of treatment, three courses of treatment were used continuously, and further consultation at one month after stopping treatment.

Chronic cervicitis is a common disease in married women. It refers to the infiltration of a large number of chronic inflammatory cells such as plasma cells and lymphocytes in the cervical stroma, accompanied by squamous metaplasia and hyperplasia of the cervical gland epithelium and stroma. It is a high risk factor for cervical cancer. Chronic cervicitis can be divided into four pathological types: cervical erosion, cervical polyp, cervical hypertrophy and cervical cyst. The most common pathological type is cervical erosion. Some patients may cause infection, bleeding, cervical stenosis, infertility and other symptoms after the treatment of cervical cryotherapy and microwave. Some patients have certain concerns. From January 2013 to December 2015, our hospital adopted the Policresulen Vaginal Suppository to treat cervical erosion with satisfactory effect. The report is as follows:

PACKAGE LABEL

Instruction for Usage of Policresulen Vaginal Suppository

Please read the instruction carefully and use the product under the advice of doctor

Warning: during pregnancy, especially in the last three months of pregnancy, any treatment of the cervix should not be used, while the treatment of the vagina and its surrounding areas can only be used when absolutely necessary.

【Name】Policresulen Vaginal Suppository

Pin yin: Jujiafenhuangquan Yindaoshuan

【Ingredients】The main component of this product is Policresulen. Its chemical name is: m-cresol sulfonic acid and formaldehyde polymer.

【Character】This product is light red to light red brown suppository.